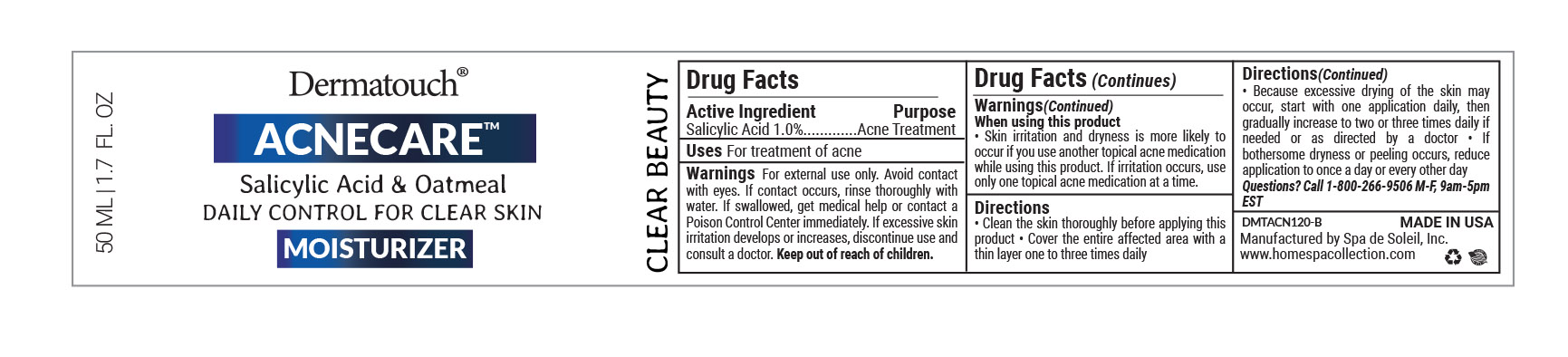 DRUG LABEL: Dermatouch Acnecare Moisturizer
NDC: 68062-9006 | Form: CREAM
Manufacturer: Spa de Soleil
Category: otc | Type: HUMAN OTC DRUG LABEL
Date: 20260121

ACTIVE INGREDIENTS: SALICYLIC ACID 0.5 mg/50 mL
INACTIVE INGREDIENTS: CAPRYLIC/CAPRIC/LAURIC TRIGLYCERIDE; WATER; CETYL ALCOHOL; GLYCERIN; OLIVE OIL

Dermatouch Acnecare Moisturizer

Active ingredient Purpose

Salicylic Acid (1.0%)..........Acne Treatment

Purpose

Acne Treatment

INDICATIONS AND USAGE

For treatment of acne

Warnings

For external use only

Avoid contact with eyes. If contact occurs, rinse thoroughly with water.

If swallowed, get medical help or contact a Poison Control Center right away. If excessive skin irritation develops or increases, discontinue use and consult a doctor. Keep out of reach of children.

Keep out of reach of children. In case of accidental ingestion, get medical help or contact a Poison Control Center right away.

When using this product

• Skin irritation and dryness is more likely to occur if you use another topical acne medication while using this product. If irritation occurs, use only one topical acne medication at a time.

Directions:

• Clean the skin thoroughly before applying this product

• Cover the entire affected area with a thin layer one to three times daily

• Because excessive drying of the skin may occur, start with one application daily, then gradually increase to two or three times daily if needed or as directed by a doctor

• If bothersome dryness or peeling occurs, reduce application to once a day or every other day

INACTIVE INGREDIENT

Other Ingredients:

Aqua, Glycerin, Caprylic/Capric Triglyceride, Cetyl Alcohol, Cetearyl Alcohol, Olea Europaea (Olive) Fruit Oil, Glyceryl Stearate SE, Carthamus Tinctorius (Safflower) Seed Oil, Cetearyl Glucoside, Xanthan Gum, Tocopheryl Acetate (Vitamin E), Disodium EDTA, Avena Sativa (Oat) Kernel Flour, Caffeine, *CO Aloe Barbadensis Leaf Powder, Sodium Hyaluronate (Hyaluronic Acid), Ascorbic Acid (Vitamin C), Retinyl Palmitate (Vitamin A), Phenoxyethanol, Ethylhexylglycerin, Fragrance. *CO – Organic